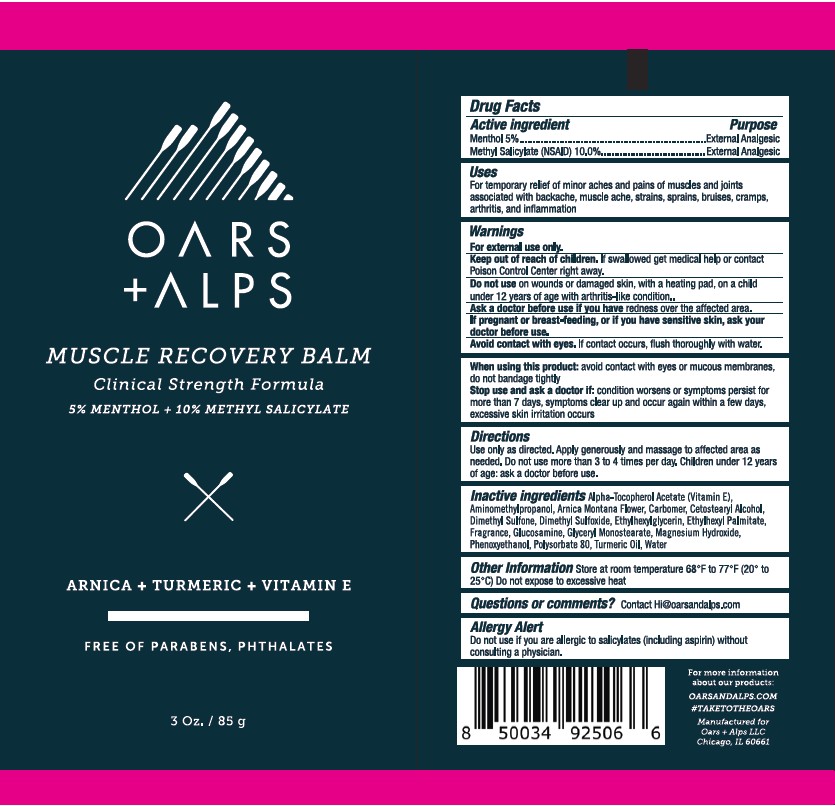 DRUG LABEL: OARS AND ALPS MUSCLE RECOVERY BALM
NDC: 52261-6300 | Form: CREAM
Manufacturer: Cosco International, Inc
Category: otc | Type: HUMAN OTC DRUG LABEL
Date: 20250408

ACTIVE INGREDIENTS: MENTHOL 0.05 kg/1 kg; METHYL SALICYLATE 0.1 kg/1 kg
INACTIVE INGREDIENTS: WATER; CARBOMER HOMOPOLYMER TYPE C; DIMETHYL SULFONE; DIMETHYL SULFOXIDE; N-ACETYLGLUCOSAMINE; GLYCERYL MONOSTEARATE; Polysorbate 80; CETOSTEARYL ALCOHOL; ARNICA MONTANA; .ALPHA.-TOCOPHEROL ACETATE, DL-; PHENOXYETHANOL; ETHYLHEXYLGLYCERIN; MAGNESIUM HYDROXIDE; AMINOMETHYLPROPANOL; TURMERIC OIL; OCTYL PALMITATE

OARS + ALPS MUSCLE RECOVERY BALM

DRUG FACTS

Menthol - 5%....................................External Analgesic
Methyl Salicylate (NSAID) – 10%.........External Analgesic

Uses:

For temporary relief of minor aches and pains of muscles and joints associated with backache, muscle ache, strains, sprains, bruises, cramps, arthritis, and inflammation

Warnings:

For external use only.

Keep out of reach of children. If swallowed, get medical help or contact a Poison Control Center right away.

Do not use on wounds or damaged skin, with a heating pad, on a child under 12 years of age with arthritis-like condition.

Ask a doctor before use if you have redness over the affected area.

If pregnant or breast-feeding, or if you have sensitive skin, ask your doctor before use

Avoid contact with eyes. If contact occurs, flush thoroughly with water.

When using this product avoid contact with eyes or mucous membranes, do not bandage tightly

Stop use and ask a doctor if: condition worsens or symptoms persist for more than 7 days, symptoms clear up and occur again within a few days, excessive skin irritation occurs

Directions:

Use only as directed. Apply generously and massage to affected area as needed. Do not use more than 3 to 4 times per day.
Children under 12 years of age: ask a doctor before use.

Inactive Ingredients:

Alpha-Tocopherol Acetate (Vitamin E), Aminomethylpropanol, Arnica Montana Flower, Carbomer, Cetostearyl Alcohol, Dimethyl Sulfone, Dimethyl Sulfoxide, Ethylhexylglycerin, Octyl Palmitate, Fragrance, Glucosamine, Glyceryl Monostearate, Magnesium Hydroxide, Phenoxyethanol, Polysorbate 80, Turmeric Oil, Water

Other Information:

Store at room temperature 68°F to 77°F (20° to 25°C)
Do not expose to excessive heat

Questions or comments?

Contact Hi@oarsandalps.com

Allergy Alert:

Do not use if you are allergic to salicylates (including aspirin) without consulting a physician.